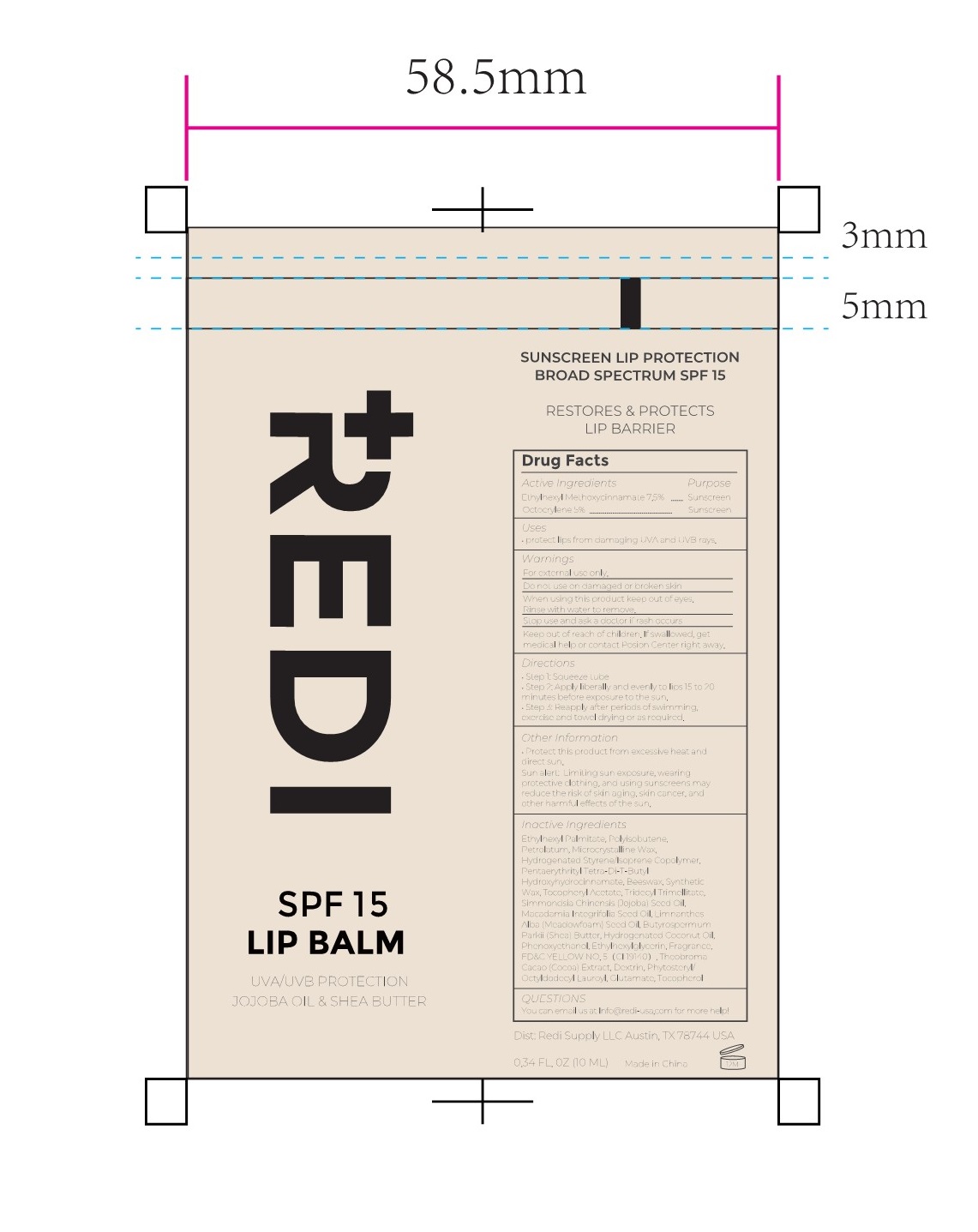 DRUG LABEL: SUNSCREEN LIP PROTECTIONBROAD SPECTRUM SPF 15
NDC: 84066-103 | Form: GEL
Manufacturer: Guangzhou Tata Biotechnology Co., Ltd.
Category: otc | Type: HUMAN OTC DRUG LABEL
Date: 20251222

ACTIVE INGREDIENTS: OCTINOXATE 7.5 mg/100 mL; OCTOCRYLENE 5 mg/100 mL
INACTIVE INGREDIENTS: ICODEXTRIN; PENTAERYTHRITOL TETRAKIS(3-(3,5-DI-TERT-BUTYL-4-HYDROXYPHENYL)PROPIONATE); COCOA; YELLOW WAX; PETROLATUM; PHENOXYETHANOL; MICROCRYSTALLINE WAX; TOCOPHEROL; ETHYLHEXYLGLYCERIN; ETHYLHEXYL PALMITATE; STYRENE/ISOPRENE COPOLYMER (28:72; 210000 MW); POLYISOBUTYLENE (1000 MW); PHYTOSTERYL/OCTYLDODECYL LAUROYL GLUTAMATE; .ALPHA.-TOCOPHEROL ACETATE; TRIDECYL TRIMELLITATE; JOJOBA OIL; SHEA BUTTER; FD&C YELLOW NO. 5; SYNTHETIC WAX (1200 MW); MACADAMIA OIL; HYDROGENATED COCONUT OIL

SUNSCREEN LIP PROTECTIONBROAD SPECTRUM SPF 15

ACTIVE INGREDIENT

Ethylhexyl Methoxycinnamate 7.5%

Octocrylene 5%

PURPOSE

Sunscreen

INDICATIONS AND USAGE

protect lips from damaging UVA and UVB rays.

WARNINGS

For external use only.

Do not use on damaged or broken skin

When using this product keep out of eyes. Rinse with water to remove.

Stop use and ask a doctor if rash occurs.

Keep out of reach of children. If product is swallowed, get medical help or contact a Poison Control Center right away.

DOSAGE AND ADMINISTRATION

Step 1:Saueeze tube.

Step 2:Apply liberally and evenly to lips 15 to 20 minutes before exposure to the sun.

Step3:Reapply after periods of swimming exercise and towel drying or as required.

OTHER SAFETY INFORMATION

Protect this product from excessive heat anddirect sun.
Sun alert: Limiting sun exposure, wearing protective clothing,and using sunscreens may reduce the risk of skin aging, skin cancer,and other harmful effects of the sun.

INACTIVE INGREDIENT

Ethylhexyl Palmitate, Polyisobutene,Petrolatum,Microcrystalline Wax,Hydrogenated Styrene/lsoprene Copolymer,PentaerythritylTetra-Di-T-ButylHydroxyhydrocinnamate,Beeswax, Synthetic Wax, Tocopheryl Acetate, Tridecyl Trimellitate,Simmondsia Chinensis (Jojoba) Seed Oil,Macadamia Integrifolia Seed Oil, Limnanthes Alba(Meadowfoam)Seed Oi,Butyrospermum Parkii (Shea) Butter, Hydrogenated Coconut Oil,Phenoxyethanol,Ethylhexylglycerin,Fragrance,FD&C YELLOW NO.5(C119140),TheobromaCacao(Cocoa)Extract,

Dextrin,Phytosteryl/OctyldodecylLauroyl, Glutamate,Tocopherol

QUESTIONS

You can email us at info@redi-usa.com for more help!